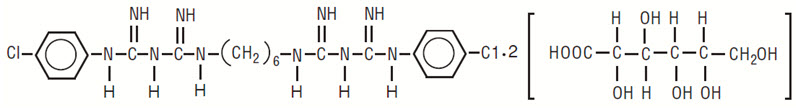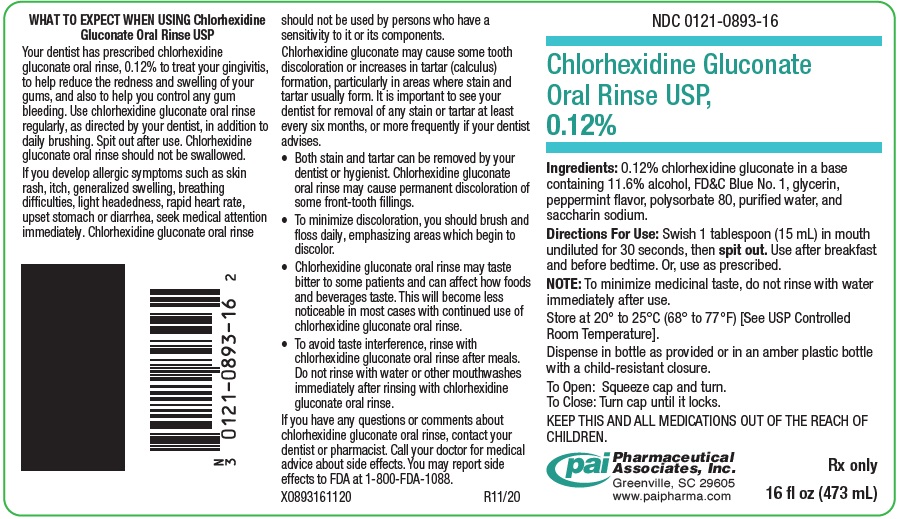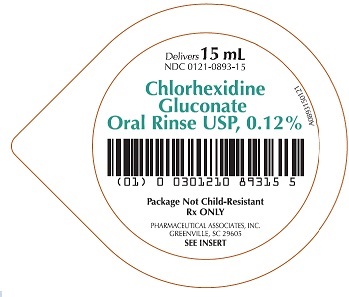 DRUG LABEL: CHLORHEXIDINE GLUCONATE
NDC: 0121-0893 | Form: RINSE
Manufacturer: PAI Holdings, LLC dba PAI Pharma
Category: prescription | Type: HUMAN PRESCRIPTION DRUG LABEL
Date: 20251202

ACTIVE INGREDIENTS: CHLORHEXIDINE GLUCONATE 1.2 mg/1 mL
INACTIVE INGREDIENTS: ALCOHOL; GLYCERIN; POLYSORBATE 80; FD&C BLUE NO. 1; WATER; SACCHARIN SODIUM

Chlorhexidine Gluconate Oral Rinse USP, 0.12%

DESCRIPTION

Chlorhexidine gluconate oral rinse USP, 0.12% is an oral rinse containing 0.12% chlorhexidine gluconate (1,1’-hexamethylene bis [5-(p-chlorophenyl) biguanide]di-D-gluconate) in a base containing 11.6% alcohol, FD&C Blue No. 1, glycerin, peppermint flavor, polysorbate 80, purified water, and saccharin sodium. Chlorhexidine Gluconate Oral Rinse, 0.12% is a near-neutral solution (pH range 5-7). Chlorhexidine gluconate is a salt of chlorhexidine and gluconic acid. Its chemical structure is:

C22H30Cl2N10•2C6H12O7 M.W. 897.72

CLINICAL PHARMACOLOGY

Chlorhexidine gluconate oral rinse, 0.12% provides antimicrobial activity during oral rinsing. The clinical significance of chlorhexidine gluconate oral rinse, 0.12% antimicrobial activities is not clear. Microbiological sampling of plaque has shown a general reduction of counts of certain assayed bacteria, both aerobic and anaerobic, ranging from 54-97% through six months use.

Use of chlorhexidine gluconate oral rinse in a six month clinical study did not result in any significant changes in bacteria resistance, overgrowth of potentially opportunistic organisms or other adverse changes in the oral microbial ecosystem. Three months after chlorhexidine gluconate oral rinse use was discontinued, the number of bacteria in plaque had returned to baseline levels and resistance of plaque bacteria to chlorhexidine gluconate was equal to that at baseline.

Pharmacokinetics

Pharmacokinetic studies with chlorhexidine gluconate oral rinse indicate approximately 30% of the active ingredient, chlorhexidine gluconate, is retained in the oral cavity following rinsing. This retained drug is slowly released into the oral fluids. Studies conducted on human subjects and animals demonstrate chlorhexidine gluconate is poorly absorbed from the gastrointestinal tract. The mean plasma level of chlorhexidine gluconate reached a peak of 0.206 µg/g in humans 30 minutes after they ingested a 300 mg dose of the drug. Detectable levels of chlorhexidine gluconate were not present in the plasma of these subjects 12 hours after the compound was administered. Excretion of chlorhexidine gluconate occurred primarily through the feces (~90%). Less than 1% of the chlorhexidine gluconate ingested by these subjects was excreted in the urine.

INDICATION

Chlorhexidine gluconate oral rinse, 0.12% is indicated for use between dental visits as part of a professional program for the treatment of gingivitis as characterized by redness and swelling of the gingivae, including gingival bleeding upon probing. Chlorhexidine gluconate oral rinse, 0.12% has not been tested among patients with acute necrotizing ulcerative gingivitis (ANUG). For patients having coexisting gingivitis and periodontitis, see PRECAUTIONS.

CONTRAINDICATIONS

Chlorhexidine gluconate oral rinse, 0.12% should not be used by persons who are known to be hypersensitive to chlorhexidine gluconate or other formula ingredients.

WARNINGS

The effect of chlorhexidine gluconate oral rinse, 0.12% on periodontitis has not been determined. An increase in supragingival calculus was noted in clinical testing in chlorhexidine gluconate oral rinse users compared with control users. It is not known if chlorhexidine gluconate use results in an increase in subgingival calculus. Calculus deposits should be removed by a dental prophylaxis at intervals not greater than six months. Anaphylaxis, as well as serious allergic reactions, have been reported during postmarketing use with dental products containing chlorhexidine. (See CONTRAINDICATIONS).

PRECAUTIONS

General

1. For patients having coexisting gingivitis and periodontitis, the presence or absence of gingival inflammation following treatment with chlorhexidine gluconate oral rinse, 0.12% should not be used as a major indicator of underlying periodontitis.

2. Chlorhexidine gluconate oral rinse, 0.12% can cause staining of oral surfaces, such as tooth surfaces, restorations, and the dorsum of the tongue. Not all patients will experience a visually significant increase in tooth staining. In clinical testing, 56% of chlorhexidine gluconate oral rinse users exhibited a measurable increase in facial anterior stain, compared to 35% of control users after six months; 15% of chlorhexidine gluconate users developed what was judged to be heavy stain, compared to 1% of control users after six months. Stain will be more pronounced in patients who have heavier accumulations of unremoved plaque.

Stain resulting from use of chlorhexidine gluconate oral rinse, 0.12% does not adversely affect health of the gingivae or other oral tissues. Stain can be removed from most tooth surfaces by conventional professional prophylactic techniques. Additional time may be required to complete the prophylaxis. Discretion should be used when prescribing to patients with anterior facial restorations with rough surfaces or margins. If natural stain cannot be removed from these surfaces by a dental prophylaxis, patients should be excluded from chlorhexidine gluconate oral rinse, 0.12% treatment if permanent discoloration is unacceptable. Stain in these areas may be difficult to remove by dental prophylaxis and on rare occasions may necessitate replacement of these restorations.

3. Some patients may experience an alteration in taste perception while undergoing treatment with chlorhexidine gluconate oral rinse. Rare instances of permanent taste alteration following chlorhexidine gluconate oral rinse use have been reported via postmarketing product surveillance.

Pregnancy

Teratogenic Effects

Reproduction studies have been performed in rats and rabbits at chlorhexidine gluconate doses up to 300 mg/kg/day and 40 mg/kg/day, respectively, and have not revealed evidence of harm to the fetus. However, adequate and well-controlled studies in pregnant women have not been done. Because animal reproduction studies are not always predictive of human response, this drug should be used during pregnancy only if clearly needed.

Nursing Mothers

It is not known whether this drug is excreted in human milk. Because many drugs are excreted in human milk, caution should be exercised when chlorhexidine gluconate oral rinse is administered to nursing women. In parturition and lactation studies with rats, no evidence of impaired parturition or of toxic effects to suckling pups was observed when chlorhexidine gluconate was administered to dams at doses that were over 100 times greater than that which would result from a person’s ingesting 30 mL of chlorhexidine gluconate oral rinse, 0.12% per day.

Pediatric Use

Clinical effectiveness and safety of chlorhexidine gluconate oral rinse, 0.12% have not been established in children under the age of 18.

Carcinogenesis, Mutagenesis, Impairment of Fertility

In a drinking water study in rats, carcinogenic effects were not observed at doses up to 38 mg/kg/day. Mutagenic effects were not observed in two mammalian in vivo mutagenesis studies with chlorhexidine gluconate. The highest doses of chlorhexidine used in a mouse dominant-lethal assay and a hamster cytogenetics test were 1000 mg/kg/day and 250 mg/kg/day, respectively. No evidence of impaired fertility was observed in rats at doses up to 100 mg/kg/day.

ADVERSE REACTIONS

The most common side effects associated with chlorhexidine gluconate oral rinses are: 1) an increase in staining of teeth and other oral surfaces; 2) an increase in calculus formation; and 3) an alteration in taste perception, see WARNINGS and PRECAUTIONS. Oral irritation and local allergy-type symptoms have been spontaneously reported as side effects associated with the use of chlorhexidine gluconate oral rinse. The following oral mucosal side effects were reported during placebo-controlled adult clinical trials: aphthous ulcer, grossly obvious gingivitis, trauma, ulceration, erythema, desquamation, coated tongue, keratinization, geographic tongue, mucocele, and short frenum. Each occurred at a frequency of less than 1%. Among postmarketing reports, the most frequently reported oral mucosal symptoms associated with chlorhexidine gluconate oral rinse are stomatitis, gingivitis, glossitis, ulcer, dry mouth, hypesthesia, glossal edema, and paresthesia. Minor irritation and superficial desquamation of the oral mucosa have been noted in patients using chlorhexidine gluconate oral rinse. There have been cases of parotid gland swelling and inflammation of the salivary glands (sialadenitis) reported in patients using chlorhexidine gluconate oral rinse.

To report SUSPECTED ADVERSE REACTIONS, contact Pharmaceutical Associates, Inc. at 1-800-845-8210 or FDA at 1-800-FDA-1088 or www.fda.gov/medwatch.

OVERDOSAGE

Ingestion of 1 or 2 ounces of chlorhexidine gluconate oral rinse, 0.12% by a small child (~10 kg body weight) might result in gastric distress, including nausea, or signs of alcohol intoxication. Medical attention should be sought if more than 4 ounces of chlorhexidine gluconate oral rinse, 0.12% is ingested by a small child or if signs of alcohol intoxication develop.

DOSAGE AND ADMINISTRATION

Chlorhexidine gluconate oral rinse, 0.12% therapy should be initiated directly following a dental prophylaxis. Patients using chlorhexidine gluconate oral rinse, 0.12% should be reevaluated and given a thorough prophylaxis at intervals no longer than six months. Recommended use is twice daily oral rinsing for 30 seconds, morning and evening after toothbrushing. Usual dosage is 15 mL of undiluted chlorhexidine gluconate oral rinse, 0.12%. Patients should be instructed to not rinse with water or other mouthwashes, brush teeth or eat immediately after using chlorhexidine gluconate oral rinse, 0.12%. Chlorhexidine gluconate oral rinse, 0.12% is not intended for ingestion and should be expectorated after rinsing.

HOW SUPPLIED

Chlorhexidine gluconate oral rinse USP, 0.12% is a clear, light blue, peppermint flavored liquid and is supplied as:

NDC 0121-0893-16: 16 fl oz (473 mL)

NDC 0121-0893-15: 15 mL unit dose cup. Case contains 40 unit dose cups of 15 mL (NDC 0121-0893-40), packaged in 4 trays of 10 unit dose cups each and 100 unit dose cups of 15 mL (NDC 0121-0893-00) packaged in 10 trays of 10 unit dose cups each.

STORAGE AND HANDLING

Store at 20° to 25°C (68° to 77°F) [See USP Controlled Room Temperature].

Rx only

Keep out of reach of children

Dispense in bottle as provided with a child-resistant closure.

MANUFACTURED BY

Pharmaceutical Associates, Inc.
Greenville, SC 29605
www.paipharma.com

R03/24

What To Expect When Using Chlorhexidine Gluconate Oral Rinse, USP 0.12%

Your dentist has prescribed chlorhexidine gluconate oral rinse, 0.12% to treat your gingivitis, to help reduce the redness and swelling of your gums, and also to help you control any gum bleeding. Use chlorhexidine gluconate oral rinse regularly, as directed by your dentist, in addition to daily brushing. Spit out after use. Chlorhexidine gluconate oral rinse should not be swallowed.

If you develop allergic symptoms such as skin rash, itch, generalized swelling, breathing difficulties, light headedness, rapid heart rate, upset stomach or diarrhea, seek medical attention immediately. Chlorhexidine gluconate oral rinse should not be used by persons who have a sensitivity to it or its components.

Chlorhexidine gluconate oral rinse may cause some tooth discoloration or increase in tartar (calculus) formation, particularly in areas where stain and tartar usually form. It is important to see your dentist for removal of any stain or tartar at least every six months or more frequently if your dentist advises.

- Both stain and tartar can be removed by your dentist or hygienist. Chlorhexidine gluconate oral rinse may cause permanent discoloration of some front-tooth fillings.
- To minimize discoloration, you should brush and floss daily, emphasizing areas which begin to discolor.
- Chlorhexidine gluconate oral rinse may taste bitter to some patients and can affect how foods and beverages taste. This will become less noticeable in most cases with continued use of chlorhexidine gluconate oral rinse.
- To avoid taste interference, rinse with chlorhexidine gluconate oral rinse after meals. Do not rinse with water or other mouthwashes immediately after rinsing with chlorhexidine gluconate oral rinse.

If you have any questions or comments about chlorhexidine gluconate oral rinse, contact your dentist or pharmacist. Call your doctor for medical advice about side effects. You may report side effects to Pharmaceutical Associates, Inc. at 1-800-845-8210 or FDA at 1-800-FDA-1088 or www.fda.gov/medwatch.

Store at 20° to 25°C (68° to 77°F) [See USP Controlled Room Temperature].

MANUFACTURED BY

Pharmaceutical Associates, Inc.
Greenville, SC 29605
www.paipharma.com

R02/21

PRINCIPAL DISPLAY PANEL - 16 oz (473 mL) Bottle Label

NDC 0121-0893-16

Chlorhexidine Gluconate
Oral Rinse USP,
0.12%

Ingredients: 0.12% chlorhexidine gluconate in a base
containing 11.6% alcohol, FD&C Blue No. 1, glycerin,
peppermint flavor, polysorbate 80, purified water, and
saccharin sodium.

Directions For Use: Swish 1 tablespoon (15 mL) in mouth
undiluted for 30 seconds, then spit out. Use after breakfast
and before bedtime. Or, use as prescribed.

NOTE: To minimize medicinal taste, do not rinse with water
immediately after use.

Store at 20° to 25°C (68° to 77°F) [See USP Controlled
Room Temperature].

Dispense in bottle as provided or in an amber plastic bottle
with a child-resistant closure.

To Open: Squeeze cap and turn.
To Close: Turn cap until it locks.

KEEP THIS AND ALL MEDICATIONS OUT OF THE REACH OF
CHILDREN.

Pharmaceutical
Associates, Inc.
Greenville, SC 29605
www.paipharma.com

Rx only

16 fl oz (473 mL)

PRINCIPAL DISPLAY PANEL - 15 mL Cup Label

Delivers 15 mL
NDC 0121-0893-15

Chlorhexidine
Gluconate
Oral Rinse USP, 0.12%

Package Not Child-Resistant
Rx ONLY

PHARMACEUTICAL ASSOCIATES, INC.
GREENVILLE, SC 29605

SEE INSERT

A0893150121